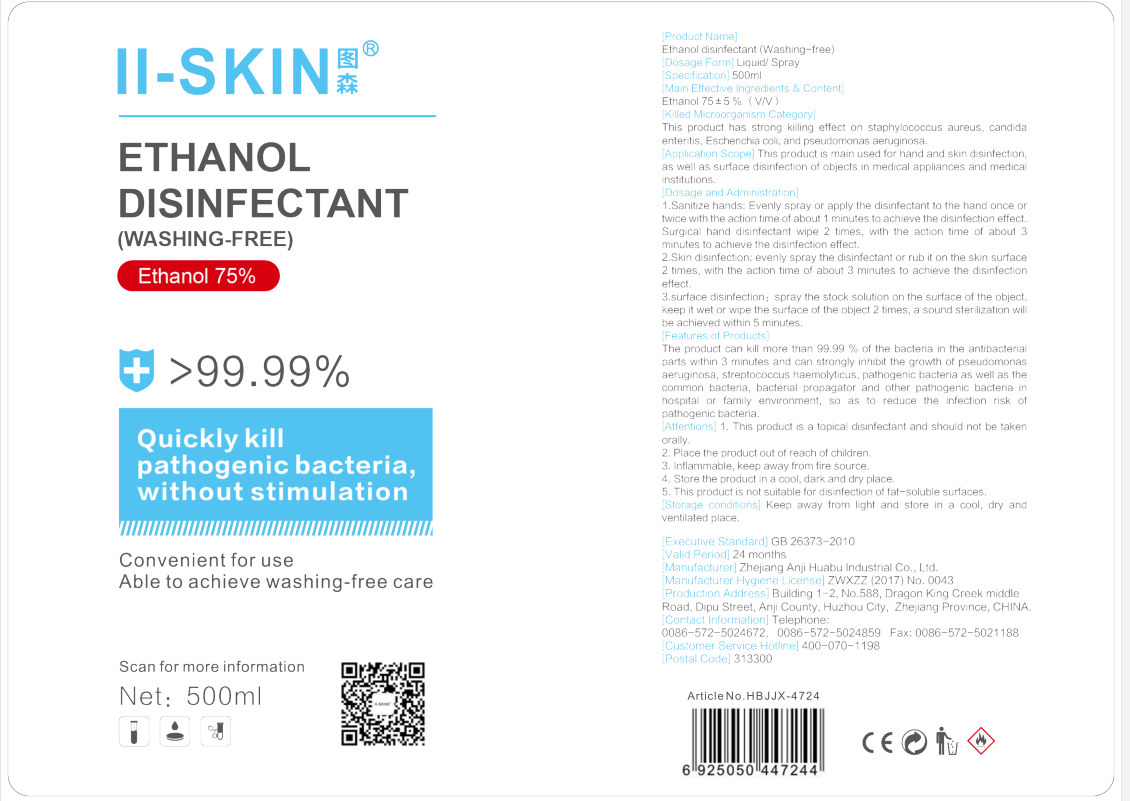 DRUG LABEL: 75% Ethanol Disinfectant (Washing-free)
NDC: 53074-003 | Form: LIQUID
Manufacturer: ZHEJIANG ANJI HUABU INDUSTRIAL CO., LTD
Category: otc | Type: HUMAN OTC DRUG LABEL
Date: 20200529

ACTIVE INGREDIENTS: ALCOHOL 375 mL/500 mL
INACTIVE INGREDIENTS: WATER

DOSAGE AND ADMINISTRATION

store in a cool, dry and ventilated place.

INACTIVE INGREDIENT

WATER

INDICATIONS AND USAGE

1.Sanitize hands: Evenly spray or apply the disinfectant to the hand once or twice with the action time of about 1 minutes to achieve the disinfection effect. Surgical hand disinfectant wipe 2 times, with the action time of about 3 minutes to achieve the disinfection

effect.
2. Skin disinfection:evenl spray the disinfectant or rub it on the skin surface 2 times,with the action time of about 3 minutes to achieve the disinfection effect.
3.surface disinfection: spray the stock solution on the surface of the object, keep it wet or wipe the surface of the object 2 times, a sound sterilization will be achieved within 5 minutes.

ACTIVE INGREDIENT

ALCOHOL

keep out of reach of children

PURPOSE

Disinfection
Sterilization

WARNINGS

1. This product is a topical disinfectant and should not be taken orally.
2. Place the product out of reach of children.
3. Inflammable, keep away from fire source.
4. Store the product in a cool, dark and dry place.
5. This product is not suitable for disinfection of fat-soluble surfaces.